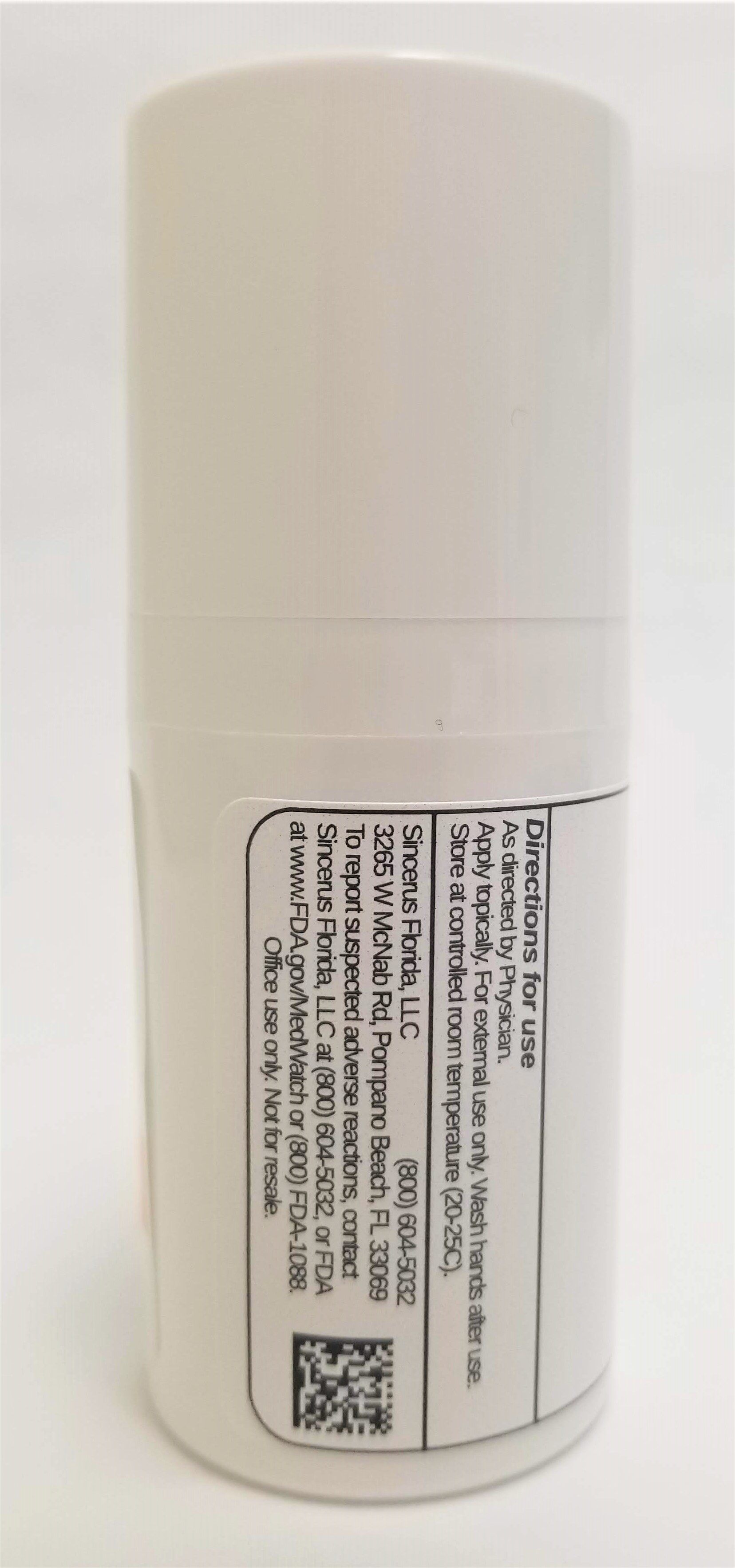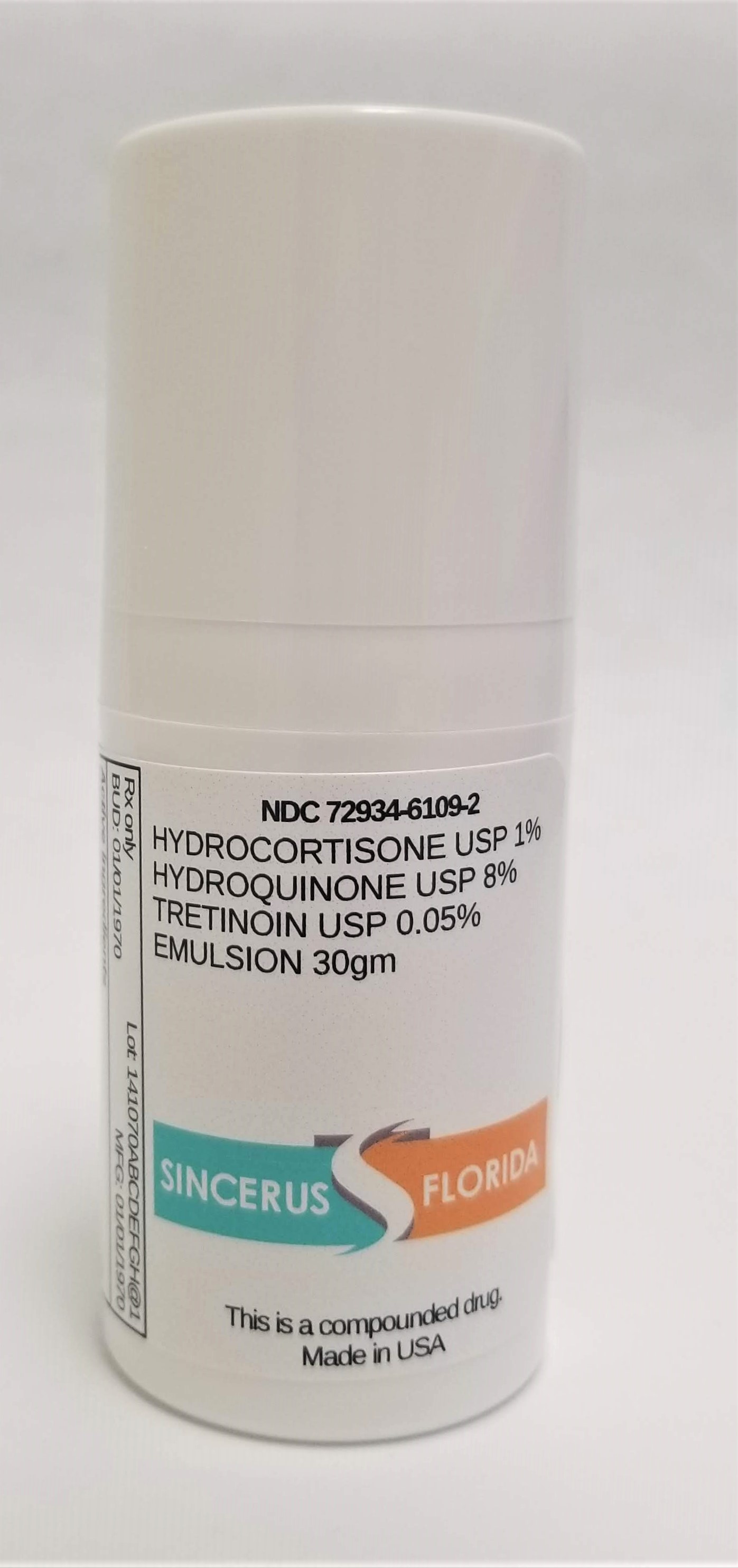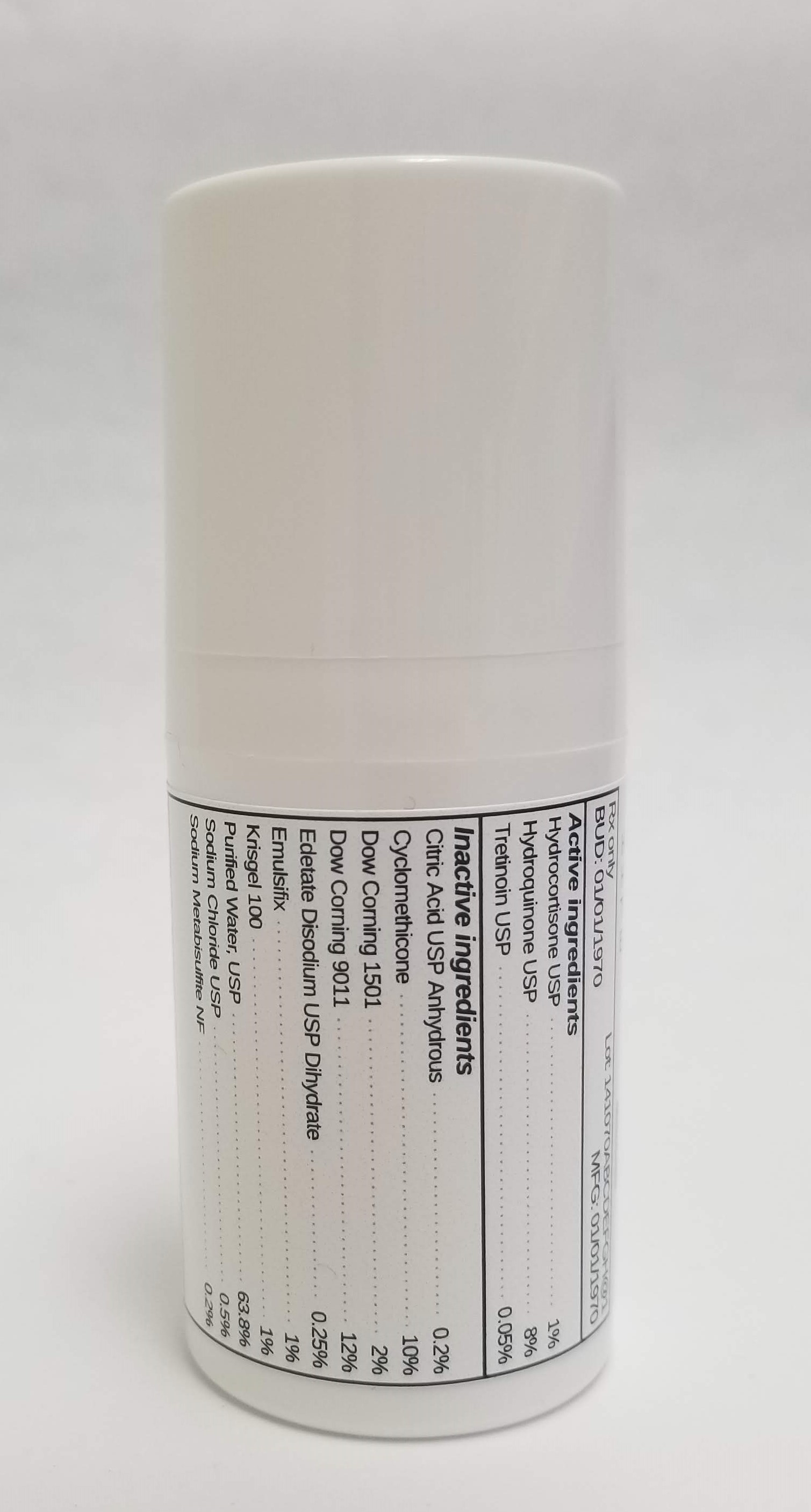 DRUG LABEL: HYDROCORTISONE 1% / HYDROQUINONE 8% / TRETINOIN 0.05%
NDC: 72934-6109 | Form: EMULSION
Manufacturer: Sincerus Florida, LLC
Category: prescription | Type: HUMAN PRESCRIPTION DRUG LABEL
Date: 20190521

ACTIVE INGREDIENTS: HYDROQUINONE 8 g/100 g; TRETINOIN 0.05 g/100 g; HYDROCORTISONE 1 g/100 g

HYDROCORTISONE 1% / HYDROQUINONE 8% / TRETINOIN 0.05%